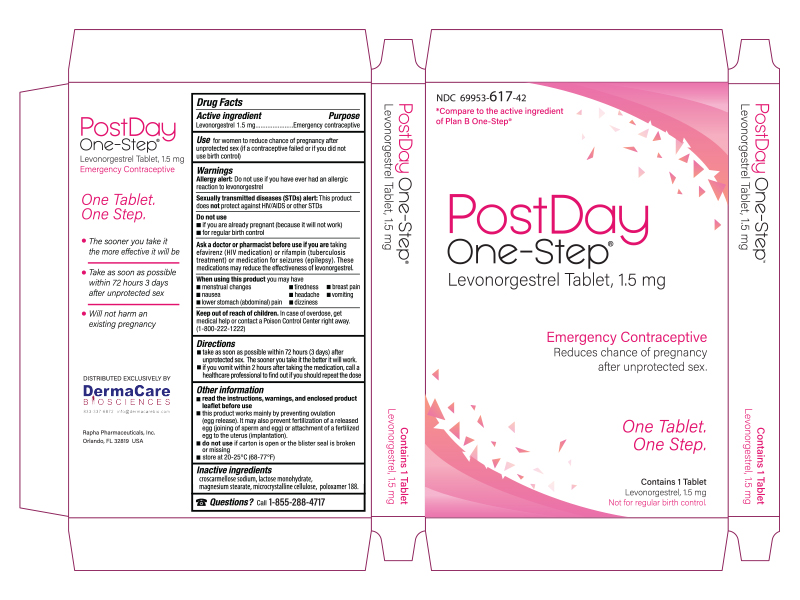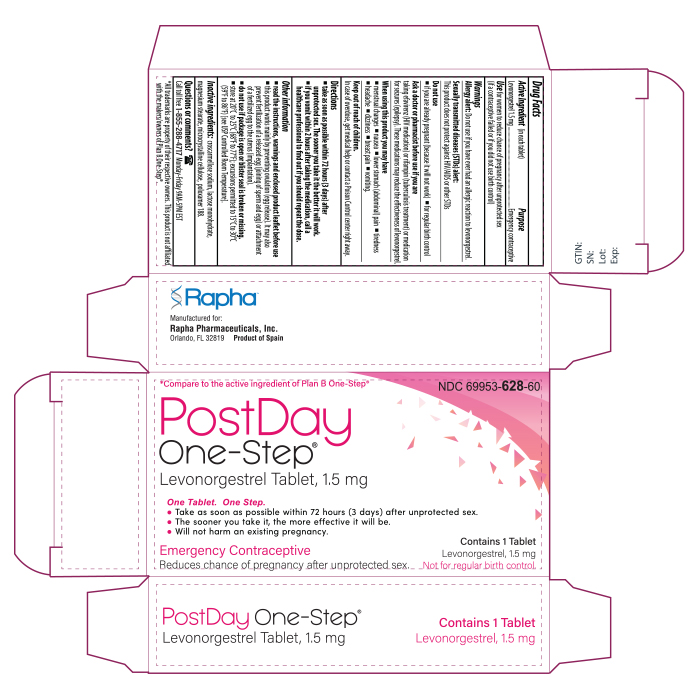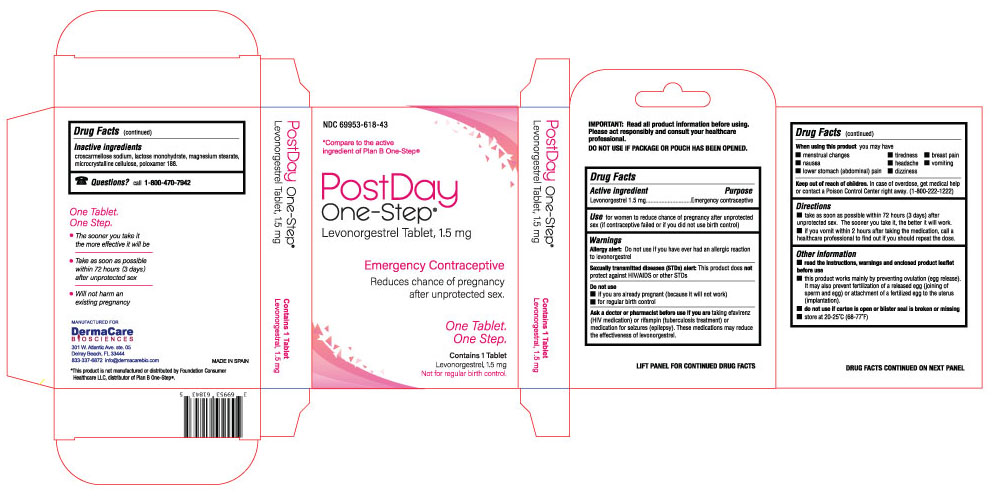 DRUG LABEL: PostDay One-Step
NDC: 69953-617 | Form: TABLET
Manufacturer: Rapha Pharmaceuticals, Inc.
Category: otc | Type: HUMAN OTC DRUG LABEL
Date: 20231121

ACTIVE INGREDIENTS: LEVONORGESTREL 1.5 mg/1.5 mg
INACTIVE INGREDIENTS: POLOXAMER 188; MAGNESIUM STEARATE; CELLULOSE, MICROCRYSTALLINE; LACTOSE MONOHYDRATE; CROSCARMELLOSE SODIUM

DRUG FACTS

Active ingredient
Levonorgestrel 1.5 mg

PURPOSE

Emergency contraceptive

USE

for women to reduce chance of pregnancy after unprotected sex (if a contraceptive failed or if you did not use birth control)

WARNINGS

Allergy alert: Do not use if you have ever had an allergic reaction to levonorgestrel
Sexually transmitted diseases (STDs) alert: This product does not protect against HIV/AIDS or other STDs

DO NOT USE

- if you are already pregnant (because it will not work)
- for regular birth control

ASK A DOCTOR OR PHARMACIST BEFORE USE IF YOU ARE

taking efavirenz (HIV medication) or rifampin (tuberculosis treatment) or medication for seizures (epilepsy). These medications may reduce the effectiveness of levonorgestrel.

WHEN USING THIS PRODUCT YOU MAY HAVE

- menstrual changes
- nausea
- lower stomach (abdominal) pain
- tiredness
- headache
- dizziness
- breast pain
- vomiting

KEEP OUT OF REACH OF CHILDREN

In case of overdose, get medical help or contact a Poison Control Center right away.

DIRECTIONS

- take as soon as possible within 72 hours (3 days) after unprotected sex. The sooner you take it the better it will work.
- if you vomit within 2 hours after taking the medication, call a healthcare professional to find out if you should repeat the dose.

OTHER INFORMATION

- read the instructions, warnings and enclosed product leaflet before use
- this product works mainly by preventing ovulation (egg release). It may also prevent fertilization of a released egg (joining of sperm and egg) or attachment of a fertilized egg to the uterus (implantation).
- do not use if package is open or blister seal is broken or missing
- store levonorgestrel tablets 1.5 mg at 20°C to 25°C (68°F to 77°F); excursions permitted to 15°C to 30°C (59°F to 86°F) [see USP Controlled Room Temperature]

INACTIVE INGREDIENTS

cellulose microcrystalline, croscarmellose sodium, lactose monohydrate, magnesium stearate, poloxamer 188

QUESTIONS?

Call 1-855-288-4717
Rapha Pharmaceuticals, Inc.
Orlando, Florida 32819 USA

PATIENT INFORMATION

Levonorgestrel Tablet, 1.5 mg
Emergency Contraceptive
One Tablet. One Step.
What You Need to Know

What is Levonorgestrel Tablets 1.5 mg?
Levonorgestrel tablets 1.5 mg is emergency contraception that helps prevent pregnancy after birth control failure or unprotected sex. It is a backup method of preventing pregnancy and should not be used as regular birth control.

What Levonorgestrel Tablets 1.5 mg is not.
Levonorgestrel tablets 1.5 mg will not work if you are already pregnant and will not affect an existing pregnancy. Levonorgestrel tablets 1.5 mg will not protect you from HIV infection (the virus that causes AIDS) and other sexually transmitted diseases (STDs).

When should I use Levonorgestrel Tablets 1.5 mg?
The sooner you take emergency contraception, the better it works. You should use Levonorgestrel tablets 1.5 mg within 72 hours (3 days) after you have had unprotected sex.

Levonorgestrel Tablets 1.5 mg is a backup or emergency method of birth control you can use when:
• your regular birth control was used incorrectly or failed
• you did not use any birth control method

When not to use Levonorgestrel Tablets 1.5 mg
Levonorgestrel Tablets 1.5 mg should not be used:
• as a regular birth control method, because it’s not as effective as regular birth control.
• if you are already pregnant, because it will not work.
• if you are allergic to levonorgestrel or any other ingredients in Levonorgestrel tablets 1.5 mg.

When should I talk to a doctor or pharmacist?
Ask a doctor or pharmacist before use if you are taking efavirenz (HIV medication) or rifampin (tuberculosis treatment) or medication for seizures (epilepsy). These medications may reduce the effectiveness of Levonorgestrel tablets 1.5 mg and increase your chance of becoming pregnant. Your doctor may prescribe another form of emergency contraception that may not be affected by these medications.

How does Levonorgestrel Tablets 1.5 mg work?
Levonorgestrel Tablets 1.5 mg is one tablet with levonorgestrel, a hormone that has been used in many birth control pills for several decades. Levonorgestrel Tablets 1.5 mg contains a higher dose of levonorgestrel than birth control pills, but works in a similar way to prevent pregnancy. It works mainly by stopping the release of an egg from the ovary. It is possible that Levonorgestrel Tablets 1.5 mg may also work by preventing fertilization of an egg (the uniting of sperm with the egg) or by preventing attachment (implantation) to the uterus (womb).

How can I get the best results from Levonorgestrel Tablets 1.5 mg?
You have 72 hours (3 days) to try to prevent pregnancy after birth control failure or unprotected sex. The sooner you take Levonorgestrel Tablets 1.5 mg, the better it works.

How effective is Levonorgestrel Tablets 1.5 mg?
If Levonorgestrel Tablets 1.5 mg is taken as directed, it can significantly decrease the chance that you will get pregnant. About 7 out of every 8 women who would have gotten pregnant will not become pregnant.

How will I know Levonorgestrel Tablets 1.5 mg worked?
You will know Levonorgestrel Tablets 1.5 mg has been effective when you get your next period, which should come at the expected time, or within a week of the expected time. If your period is delayed beyond 1 week, it is possible you may be pregnant. You should get a pregnancy test and follow up with your healthcare professional.

Will I experience any side effects?
• some women may have changes in their period, such as a period that is heavier or lighter or a period that is early or late. If your period is more than a week late, you may be pregnant.
• if you have severe abdominal pain, you may have an ectopic pregnancy, and should get immediate medical attention.
• when used as directed, Levonorgestrel Tablets 1.5 mg is safe and effective. Side effects may include changes in your period, nausea, lower stomach (abdominal) pain, tiredness, headache, dizziness, and breast tenderness.
• if you vomit within 2 hours of taking the medication, call a healthcare professional to find out if you should repeat the dose.

What if I still have questions about Levonorgestrel Tablets 1.5 mg?
If you have questions or need more information, call our toll-free number at 1-855-288-4717

Other Information

Keep out of reach of children:
In case of overdose, get medical help or contact a Poison Control Center right away at 1-800-222-1222.

Do not use if the blister seal is opened.

Store levonorgestrel tablets 1.5 mg at 20°C to 25°C (68°F to 77°F); excursions permitted to 15°C to 30°C (59°F to 86°F) [see USP Controlled Room Temperature].

Active ingredient: levonorgestrel 1.5 mg

Inactive ingredients: cellulose microcrystalline, croscarmellose sodium, lactose monohydrate, magnesium stearate, poloxamer 188

1-855-288-4717

www.raphpharma.com

If you are sexually active, you should see a healthcare provider for routine checkups. Your healthcare provider will talk to you about and, if necessary, test you for sexually transmitted diseases, teach you about effective methods of routine birth control, and answer any other questions you may have.

Rapha Pharmaceuticals, Inc.
Orlando, Florida 32819 USA

PACKAGE LABEL-PRINCIPAL DISPLAY PANEL - 1.5 MG (1 TABLET CARTON LABEL) - NDC 69953-628-60

Levonorgestrel Tablets
(levonorgestrel) tablets 1.5 mg
Emergency contraceptive
Reduces chance of pregnancy after unprotected sex.
Not for regular birth control.
Rapha Pharmaceuticals, Inc.

PACKAGE LABEL-PRINCIPAL DISPLAY PANEL - 1.5 MG (1 TABLET CARTON LABEL) - NDC 69953-617-42

Levonorgestrel Tablets
(levonorgestrel) tablets 1.5 mg
Emergency contraceptive
Reduces chance of pregnancy after unprotected sex.
Not for regular birth control.
Rapha Pharmaceuticals, Inc.

PACKAGE LABEL-PRINCIPAL DISPLAY PANEL - 1.5 MG (1 TABLET CARTON LABEL) - NDC 69953-618-43

Levonorgestrel Tablets
(levonorgestrel) tablets 1.5 mg
Emergency contraceptive
Reduces chance of pregnancy after unprotected sex.
Not for regular birth control.
Rapha Pharmaceuticals, Inc.